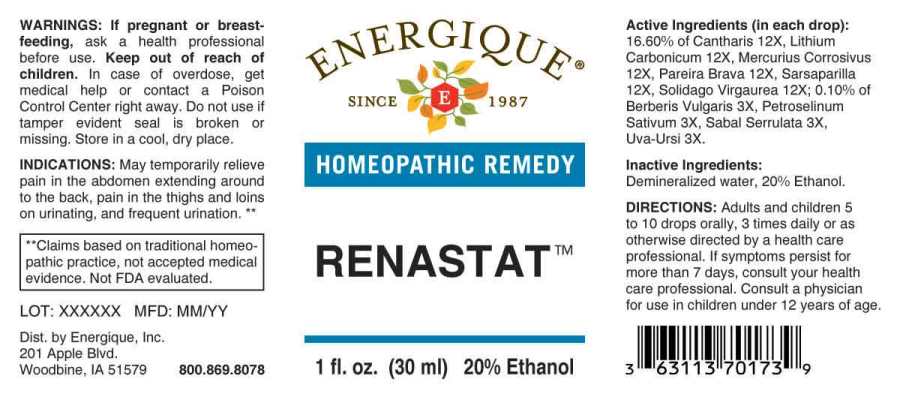 DRUG LABEL: Renastat
NDC: 44911-0033 | Form: LIQUID
Manufacturer: Energique, Inc.
Category: homeopathic | Type: HUMAN OTC DRUG LABEL
Date: 20241030

ACTIVE INGREDIENTS: SAW PALMETTO 3 [hp_X]/1 mL; LYTTA VESICATORIA 12 [hp_X]/1 mL; LITHIUM CARBONATE 12 [hp_X]/1 mL; MERCURIC CHLORIDE 12 [hp_X]/1 mL; BERBERIS VULGARIS ROOT BARK 3 [hp_X]/1 mL; PETROSELINUM CRISPUM WHOLE 3 [hp_X]/1 mL; ARCTOSTAPHYLOS UVA-URSI LEAF 3 [hp_X]/1 mL; CHONDRODENDRON TOMENTOSUM ROOT 12 [hp_X]/1 mL; SMILAX ORNATA ROOT 12 [hp_X]/1 mL; SOLIDAGO VIRGAUREA FLOWERING TOP 12 [hp_X]/1 mL
INACTIVE INGREDIENTS: WATER; ALCOHOL

DRUG FACTS:

ACTIVE INGREDIENTS:

(in each drop): 16.60% of Cantharis 12X, Lithium Carbonicum 12X, Mercurius Corrosivus 12X, Pareira Brava 12X, Sarsaparilla 12X, Solidago Virgaurea 12X; 0.10% of Berberis Vulgaris 3X, Petroselinum Sativum 3X, Sabal Serrulata 3X, Uva Ursi 3X.

INDICATIONS:

May temporarily relieve pain in the abdomen extending around to the back, pain in the thighs and loins on urinating and frequent urination.**

**Claims based on traditional homeopathic practice, not accepted medical evidence. Not FDA evaluated.

WARNINGS:

If pregnant or breast-feeding, ask a health professional before use.

Keep out of reach of children. In case of overdose, get medical help or contact a Poison Control Center right away.

Do not use if tamper evident seal is broken or missing. Store in a cool, dry place.

DIRECTIONS:

Adults and children 5 to 10 drops orally, 3 times daily or as otherwise directed by a health care professional. If symptoms persist for more than 7 days, consult your health care professional. Consult a physician for use in children under 12 years of age.

INACTIVE INGREDIENTS:

Demineralized water, 20% Ethanol.

Keep out of reach of children. In case of overdose, get medical help or contact a Poison Control Center right away.

INDICATIONS:

May temporarily relieve pain in the abdomen extending around to the back, pain in the thighs and loins on urinating and frequent urination.**

**Claims based on traditional homeopathic practice, not accepted medical evidence. Not FDA evaluated.

QUESTIONS

Dist. by Energique, Inc.

201 Apple Blvd

Woodbine, IA 51579 800.869.8078

PACKAGE LABEL DISPLAY:

ENERGIQUE

since 1987

HOMEOPATHIC REMEDY

RENASTAT

1 fl. oz. (30 ml)